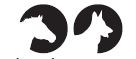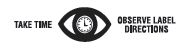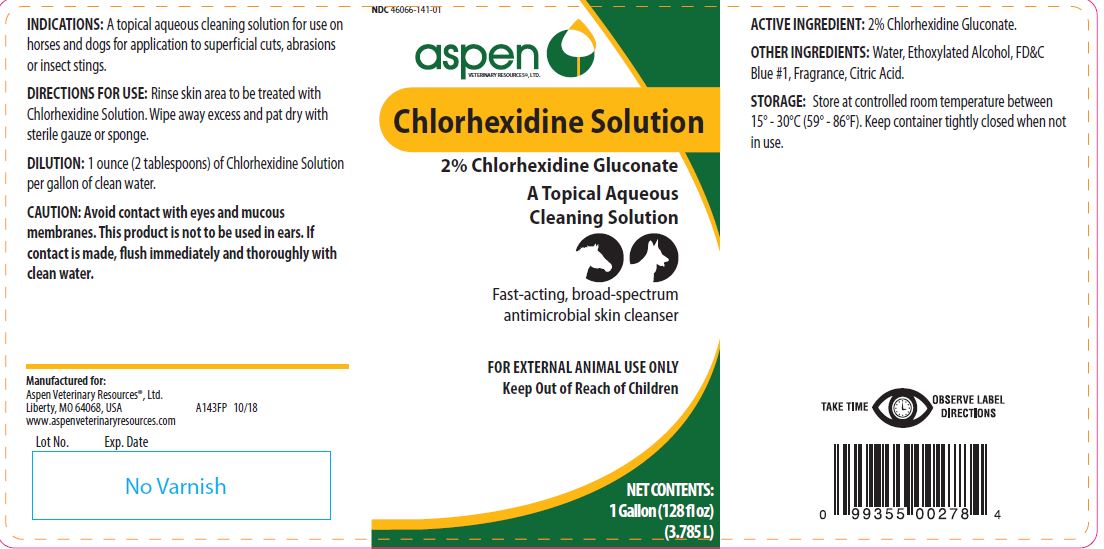 DRUG LABEL: Chlorhexidine
NDC: 46066-141 | Form: SOLUTION
Manufacturer: Aspen Veterinary
Category: animal | Type: OTC ANIMAL DRUG LABEL
Date: 20191014

ACTIVE INGREDIENTS: CHLORHEXIDINE GLUCONATE 99.0 g/1 L

Chlorhexidine Solution

PURPOSE

2% Chlorhexidine Gluconate

A Topical Aqueous Cleaning Solution

Fast-acting, broad-spectrum antimicrobial skin cleanser

KEEP OUT OF REACH OF CHILDREN

FOR EXTERNAL ANIMAL USE ONLY
Keep Out of Reach of Children

INDICATIONS:

A topical aqueous cleaning solution for use on horses and dogs for application to superficial cuts, abrasions or insect stings.

DIRECTIONS FOR USE:

Rinse skin area to be treated with Chlorhexidine Solution. Wipe away excess and pat dry with sterile gauze or sponge.

DILUTION:

1 ounce (2 tablespoons) of Chlorhexidine Solution per gallon of clean water.

CAUTION:

Avoid contact with eyes and mucous membranes. This product is not to be used in ears. If contact is made, flush immediately and thoroughly with clean water.

ACTIVE INGREDIENT:

2% Chlorhexidine Gluconate.

OTHER INGREDIENTS:

Water, Ethoxylated Alcohol, FD&C Blue #1, Fragrance, Citric Acid.

STORAGE:

Store at controlled room temperature between 15° - 30°C (59° - 86°F). Keep container tightly closed when not in use.

NET CONTENTS:

1 Gallon (128 fl oz) (3.785 L)

INFORMATION FOR OWNERS/CAREGIVERS

Manufactured for:
Aspen Veterinary Resources®, Ltd.
Liberty, MO 64068, USA A143FP 10/18
www.aspenveterinaryresources.com